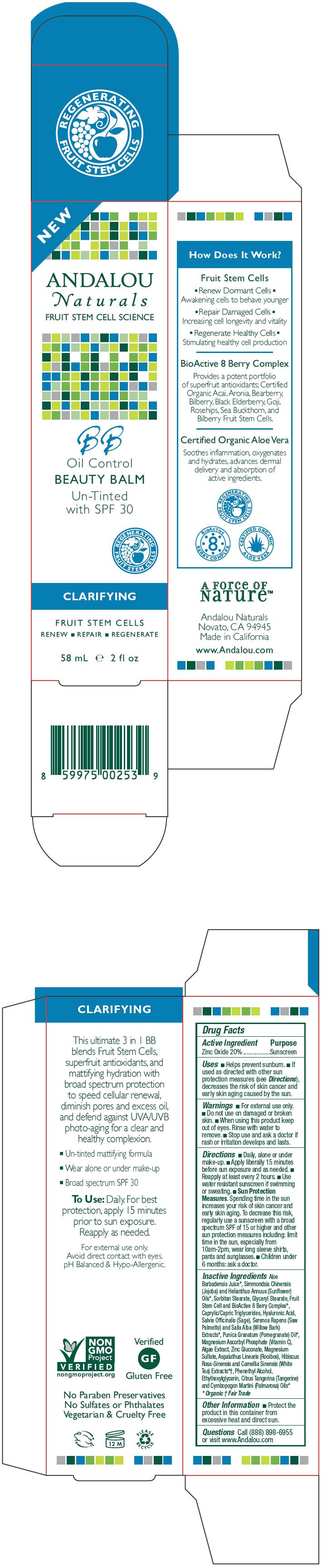 DRUG LABEL: Andalou BB Untinted with SPF-30
NDC: 55560-0101 | Form: LOTION
Manufacturer: Andalou naturals
Category: otc | Type: HUMAN OTC DRUG LABEL
Date: 20130201

ACTIVE INGREDIENTS: Zinc Oxide 20 g/100 mL
INACTIVE INGREDIENTS: glyceryl monostearate; sage; saw palmetto; willow bark; pomegranate seed oil; aloe vera leaf; zinc gluconate; medium-chain triglycerides; sorbitan monostearate; mandarin oil; magnesium sulfate; helianthus annuus flowering top; jojoba oil; tocopherol; magnesium ascorbyl phosphate; hyaluronate sodium; palmarosa oil; phenylethyl alcohol; ethylhexylglycerin

Andalou BB Untinted with SPF-30

Drug Facts

Active Ingredient

Zinc Oxide 20%

Purpose

Sunscreen

Uses

- Helps prevent sunburn.
- If used as directed with other sun protection measures (see Directions), decreases the risk of skin cancer and early skin aging caused by the sun.

Warnings

- For external use only.
- Do not use on damaged or broken skin.

- When using this product keep out of eyes. Rinse with water to remove.

- Stop use and ask a doctor if rash or irritation develops and lasts.

Directions

- Daily, alone or under make-up.
- Apply liberally 15 minutes before sun exposure and as needed.
- Reapply at least every 2 hours.
- Use water resistant sunscreen if swimming or sweating.
- Sun Protection Measures. Spending time in the sun increases your risk of skin cancer and early skin aging. To decrease this risk, regularly use a sunscreen with a broad spectrum SPF of 15 or higher and other sun protection measures including: limit time in the sun, especially from 10am-2pm, wear long sleeve shirts, pants and sunglasses.
- Children under 6 months: ask a doctor.

Inactive Ingredients

Aloe Barbadensis Juice [Organic] , Simmondsia Chinensis (Jojoba) and Helianthus Annuus (Sunflower) Oils, Sorbitan Stearate, Glyceryl Stearate, Fruit Stem Cell and BioActive 8 Berry Complex, Caprylic/Capric Triglycerides, Hyaluronic Acid, Salvia Officinalis (Sage), Serenoa Rapens (Saw Palmetto) and Salix Alba (Willow Bark) Extracts, Punica Granatum (Pomegranate) Oil, Magnesium Ascorbyl Phosphate (Vitamin C), Algae Extract, Zinc Gluconate, Magnesium Sulfate, Aspalathus Linearis (Rooibos), Hibiscus Rosa-Sinensis and Camellia Sinensis (White Tea) Extracts [Fair Trade] , Phenethyl Alcohol, Ethylhexylglycerin, Citrus Tangerina (Tangerine) and Cymbopogon Martini (Palmarosa) Oils

Other Information

- Protect the product in this container from excessive heat and direct sun.

Questions

Call (888) 898-6955 or visit www.Andalou.com

PRINCIPAL DISPLAY PANEL - 58 mL Tube Carton

NEW

ANDALOU
Naturals
FRUIT STEM CELL SCIENCE

BB
Oil Control
BEAUTY BALM
Un-Tinted
with SPF 30

REGENERATING
FRUIT STEM CELLS

CLARIFYING

FRUIT STEM CELLS
RENEW ■ REPAIR ■ REGENERATE

58 mL e 2 fl oz